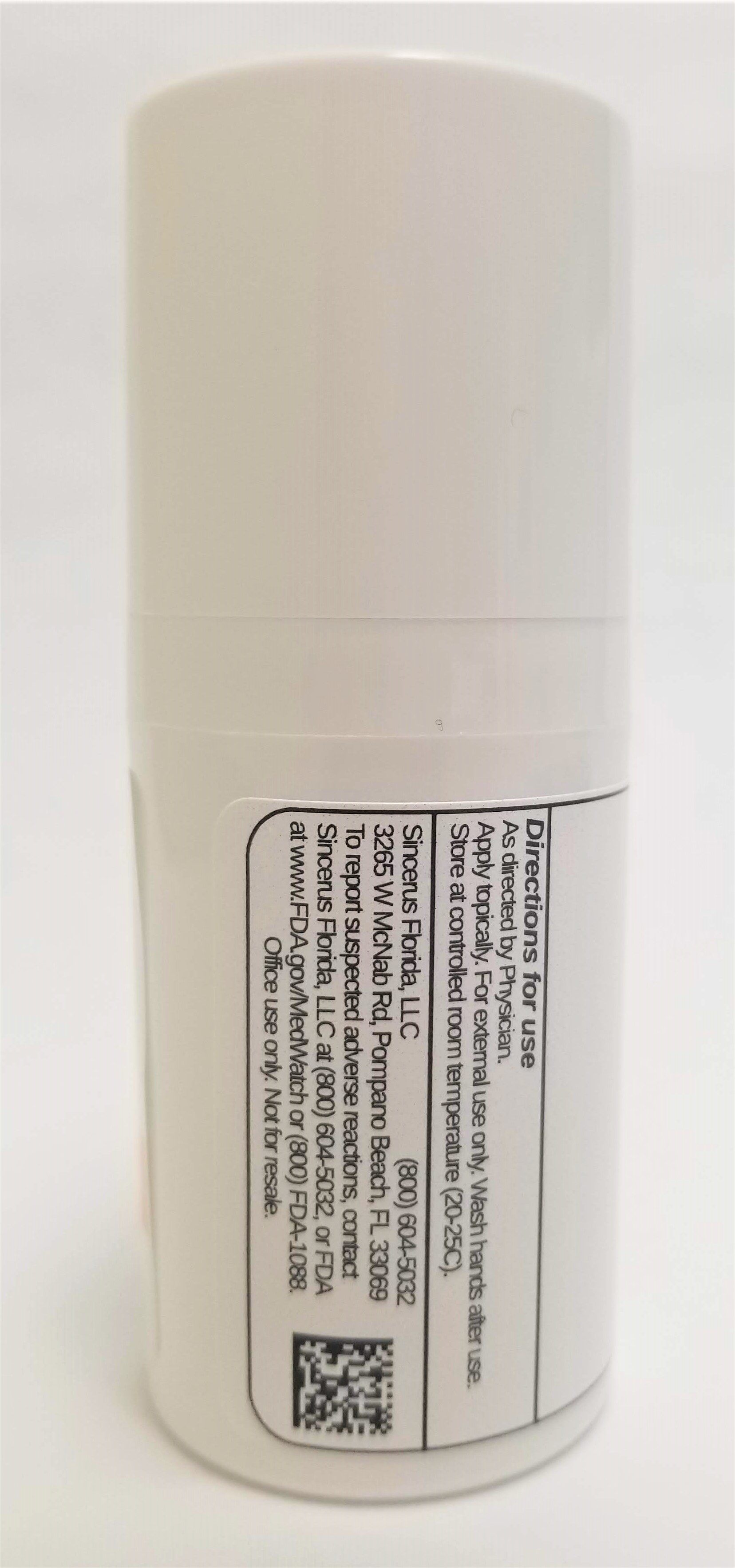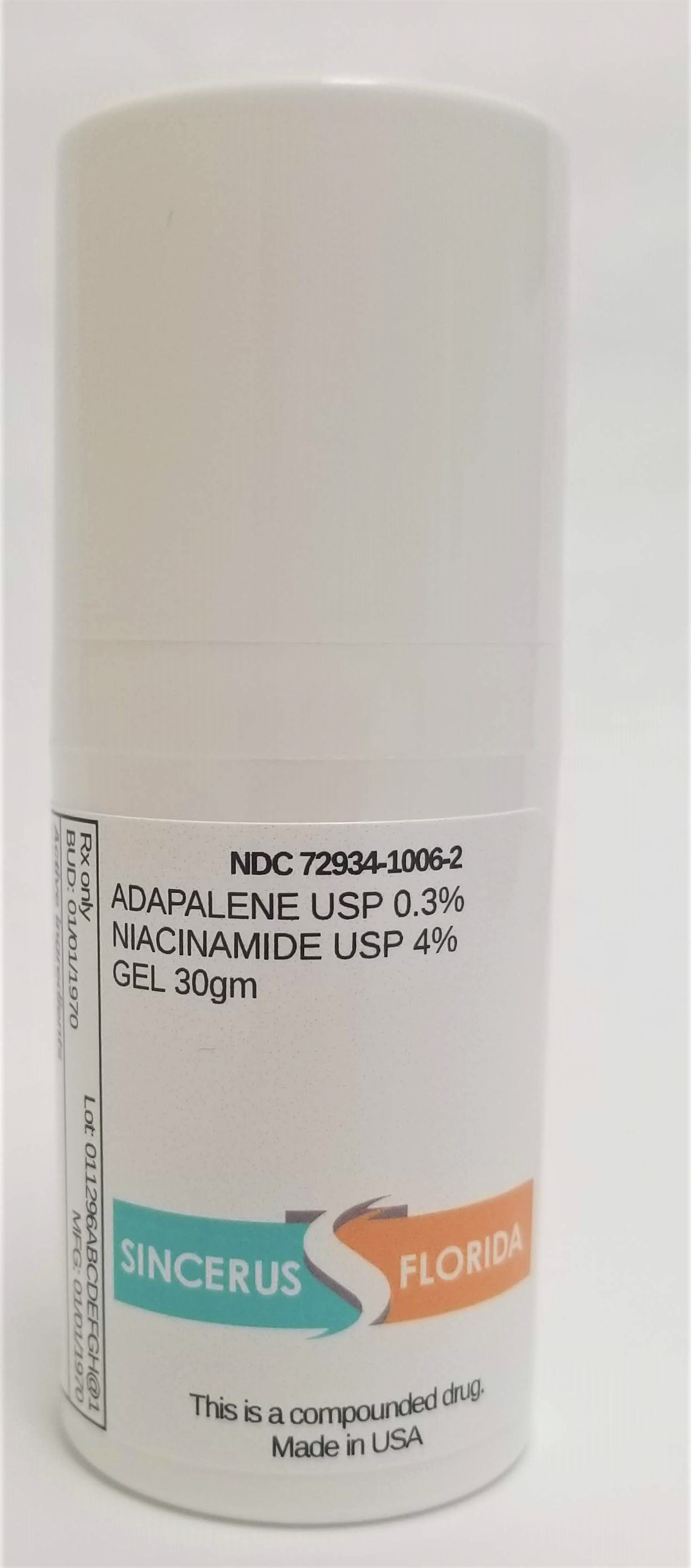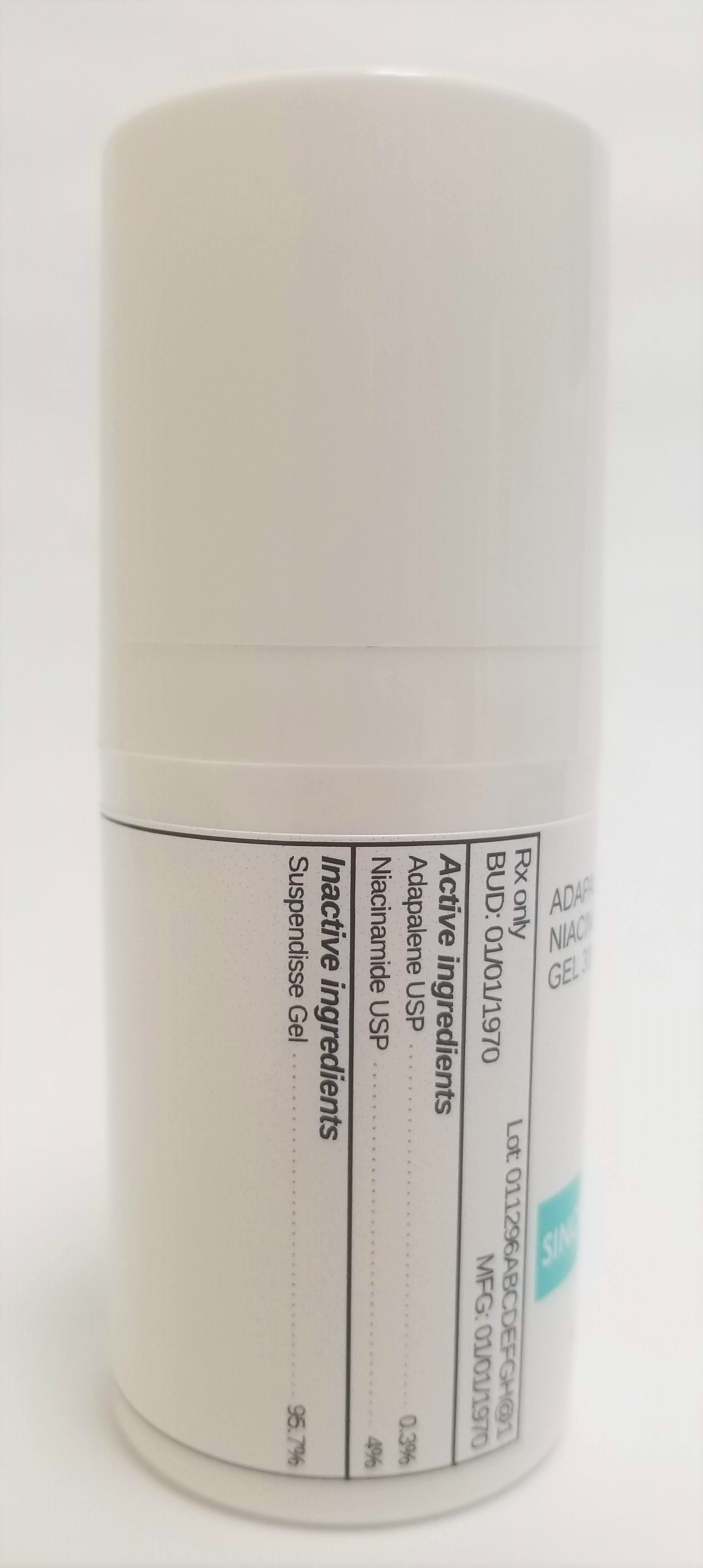 DRUG LABEL: ADAPALENE 0.3% / NIACINAMIDE 4%
NDC: 72934-1006 | Form: GEL
Manufacturer: Sincerus Florida, LLC
Category: prescription | Type: HUMAN PRESCRIPTION DRUG LABEL
Date: 20190509

ACTIVE INGREDIENTS: ADAPALENE 0.3 g/100 g; NIACINAMIDE 4 g/100 g

ADAPALENE 0.3% / NIACINAMIDE 4%